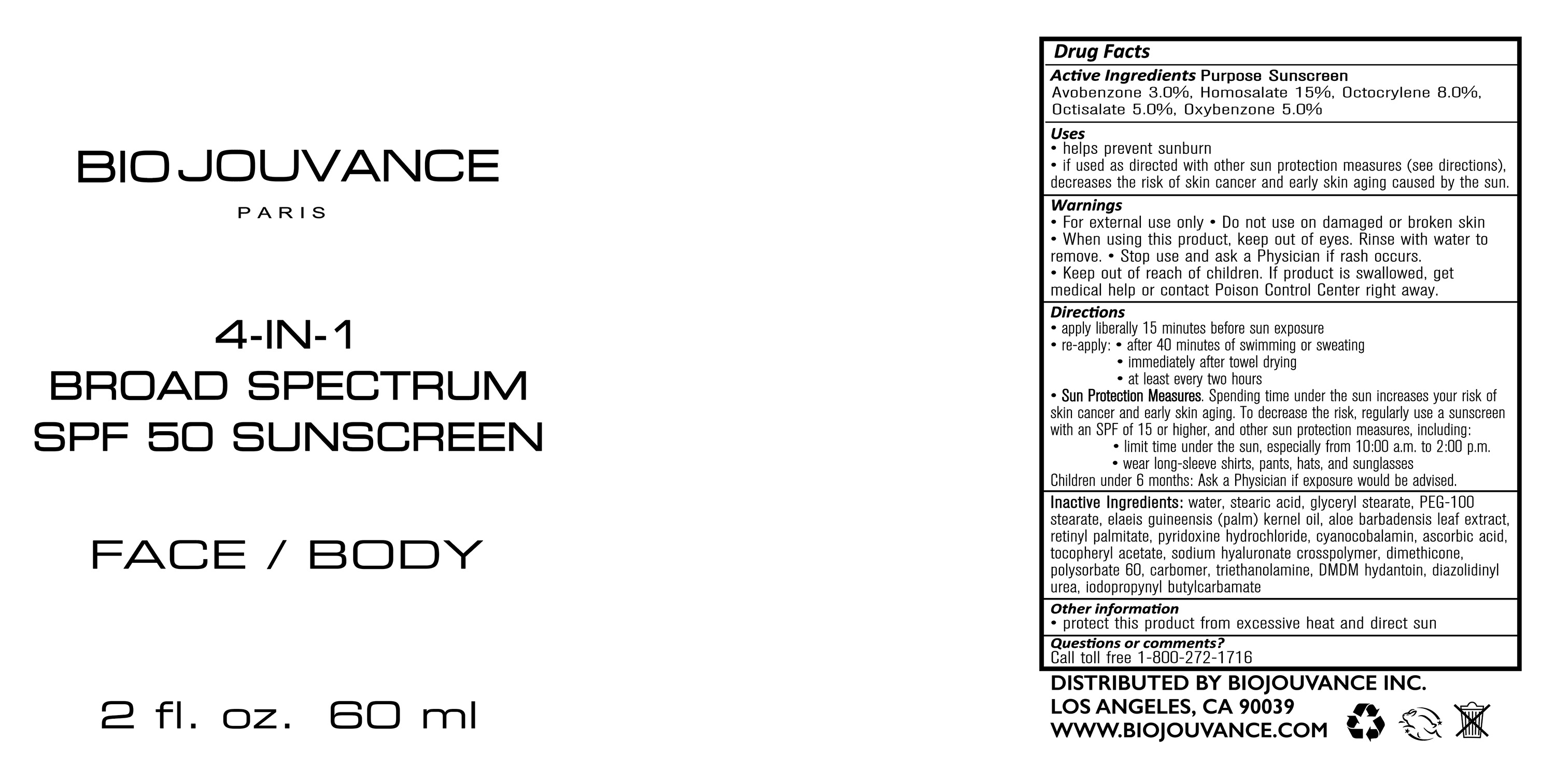 DRUG LABEL: 4-IN-1 Broad Spectrum SPF 50 Sunscreen
NDC: 80030-001 | Form: CREAM
Manufacturer: Bio Jouvance
Category: otc | Type: HUMAN OTC DRUG LABEL
Date: 20200819

ACTIVE INGREDIENTS: HOMOSALATE 15 g/100 mL; OCTOCRYLENE 8 g/100 mL; OCTISALATE 5 g/100 mL; OXYBENZONE 5 g/100 mL; AVOBENZONE 3 g/100 mL
INACTIVE INGREDIENTS: PEG-100 STEARATE; ASCORBIC ACID; WATER; CARBOMER HOMOPOLYMER, UNSPECIFIED TYPE; TROLAMINE; IODOPROPYNYL BUTYLCARBAMATE; STEARIC ACID; PALM KERNEL OIL; VITAMIN A PALMITATE; POLYSORBATE 60; GLYCERYL MONOSTEARATE; ALOE VERA LEAF; PYRIDOXINE HYDROCHLORIDE; DMDM HYDANTOIN; DIAZOLIDINYL UREA; CYANOCOBALAMIN; .ALPHA.-TOCOPHEROL ACETATE; DIMETHICONE

4-IN-1 Broad Spectrum SPF 50 Sunscreen

ACTIVE INGREDIENT

Purpose Sunscreen

Avobenzone 3.0%, Homosalate 15%, Octocrylene 8.0%, Octisalate 5.0%, Oxybenzone 5.0%

Uses

helps prevent sunburn

if used as directed with other sun protection measures (see directions), decrease the risk of skin cancer and early skin aging caused by the sun.

Keep out of reach of children. If product is swallowed, get medical help or contact Poison Control Center right away.

Stop use and ask a Physician if rash occurs.

WARNINGS

For external use only. Do not used on damaged or broken skin. When using this product, keep out of eyes. Rinse with water to remove.

DOSAGE AND ADMINISTRATION

- apply liberally 15 minutes before sun exposure
- re-apply:
- after 40 minutes of swimming or sweating
- immediately after towel drying
- at least every two hours
- Sun Protection Meaures. Spending time under the sun increases your risk of skin cancer and early skin aging. To decrease the risk, regurlarly use a sunscreen with an SPF of 15 or higher, and other sun protection meaures, including:
- limit time under the sun, especially from 10:00 a.m. to 2:00 p.m.
- wear long-sleeve shirts, pants, hats, and sunglasses
- Children under 6 months: Ask a Physician if exposure would be advised.

INACTIVE INGREDIENT

water, stearic acid, glyceryl stearate, PEG-100 stearate, elaeis guineensis kernel oil, aloe barbadensis leaft ectract, retinyl palmitate, pyridoxine hydrochloride cyanocobalamin, ascorbic acid, tocopheryl acetate, sodium hyaluronate crosspolymer, dimethicone, polysorbate 60, carbomer, triethanolamine, DMDM hydantoin, diazolidinyl urea, iodopropynyl butylcarbamate

OTHER SAFETY INFORMATION

protect this product from excessive heat and direct sun

Questions or comments?

Call toll free 1-800-272-1716

PACKAGE LABEL

BIO JOUVANCE

PARIS

4-in-1 BROAD SPECTRUM SPF 50 SUNSCREEN

FACE/BODY

2 FL. OZ. 60 ml

DISTRIBUTED BY BIOJOUVANCE INC.

LOS ANGELES, CA 90039

WWW.BIOJOUVANCE.COM